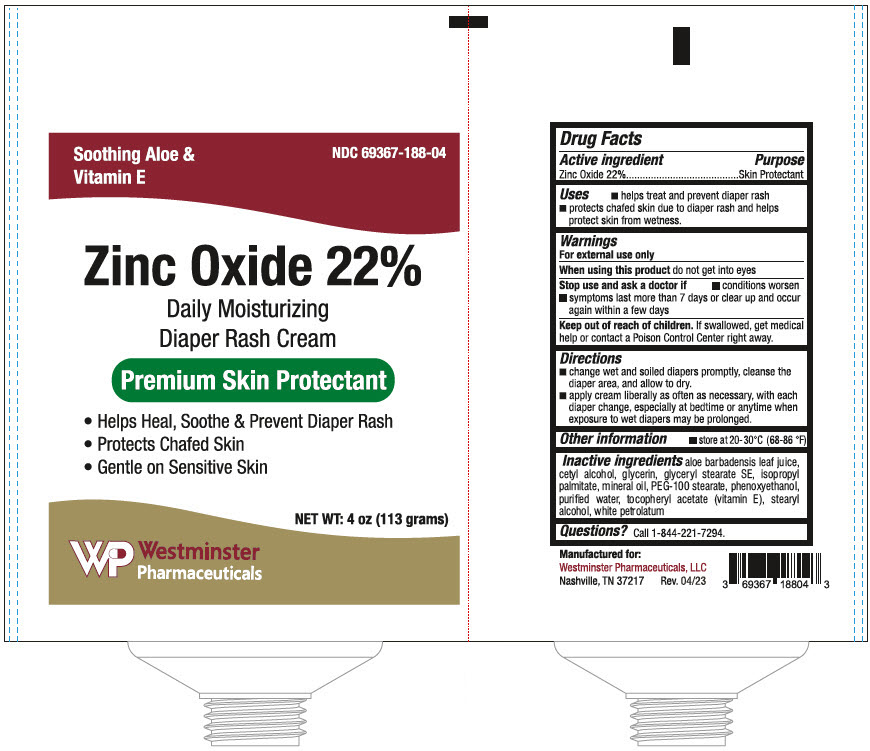 DRUG LABEL: Zinc Oxide
NDC: 69367-188 | Form: CREAM
Manufacturer: Westminster Pharmaceuticals, LLC
Category: otc | Type: HUMAN OTC DRUG LABEL
Date: 20250708

ACTIVE INGREDIENTS: ZINC OXIDE 22 g/100 g
INACTIVE INGREDIENTS: CETYL ALCOHOL; MINERAL OIL; ALOE VERA LEAF; GLYCERIN; WATER; STEARYL ALCOHOL; .ALPHA.-TOCOPHEROL ACETATE; PETROLATUM; GLYCERYL STEARATE SE; ISOPROPYL PALMITATE; PEG-100 MONOSTEARATE; PHENOXYETHANOL

Zinc Oxide

Drug Facts

Active ingredient

Zinc Oxide 22%

Purpose

Skin Protectant

Uses

- helps treat and prevent diaper rash
- protects chafed skin due to diaper rash and helps protect skin from wetness.

Warnings

For external use only

When using this product do not get into eyes

Stop use and ask a doctor if

- conditions worsen
- symptoms last more than 7 days or clear up and occur again within a few days

Keep out of reach of children. If swallowed, get medical help or contact a Poison Control Center right away.

Directions

- change wet and soiled diapers promptly, cleanse the diaper area, and allow to dry.
- apply cream liberally as often as necessary, with each diaper change, especially at bedtime or anytime when exposure to wet diapers may be prolonged.

Other information

- store at 20-30°C (68-86 °F)

Inactive ingredients

aloe barbadensis leaf juice, cetyl alcohol, glycerin, glyceryl stearate SE, isopropyl palmitate, mineral oil, PEG-100 stearate, phenoxyethanol, purified water, tocopheryl acetate (vitamin E), stearyl alcohol, white petrolatum

Questions?

Call 1-844-221-7294.

PRINCIPAL DISPLAY PANEL - 113 gram Tube Label

Soothing Aloe &
Vitamin E

NDC 69367-188-04

Zinc Oxide 22%

Daily Moisturizing
Diaper Rash Cream

Premium Skin Protectant

- Helps Heal, Soothe & Prevent Diaper Rash
- Protects Chafed Skin
- Gentle on Sensitive Skin

NET WT: 4 oz (113 grams)

Westminster
Pharmaceuticals